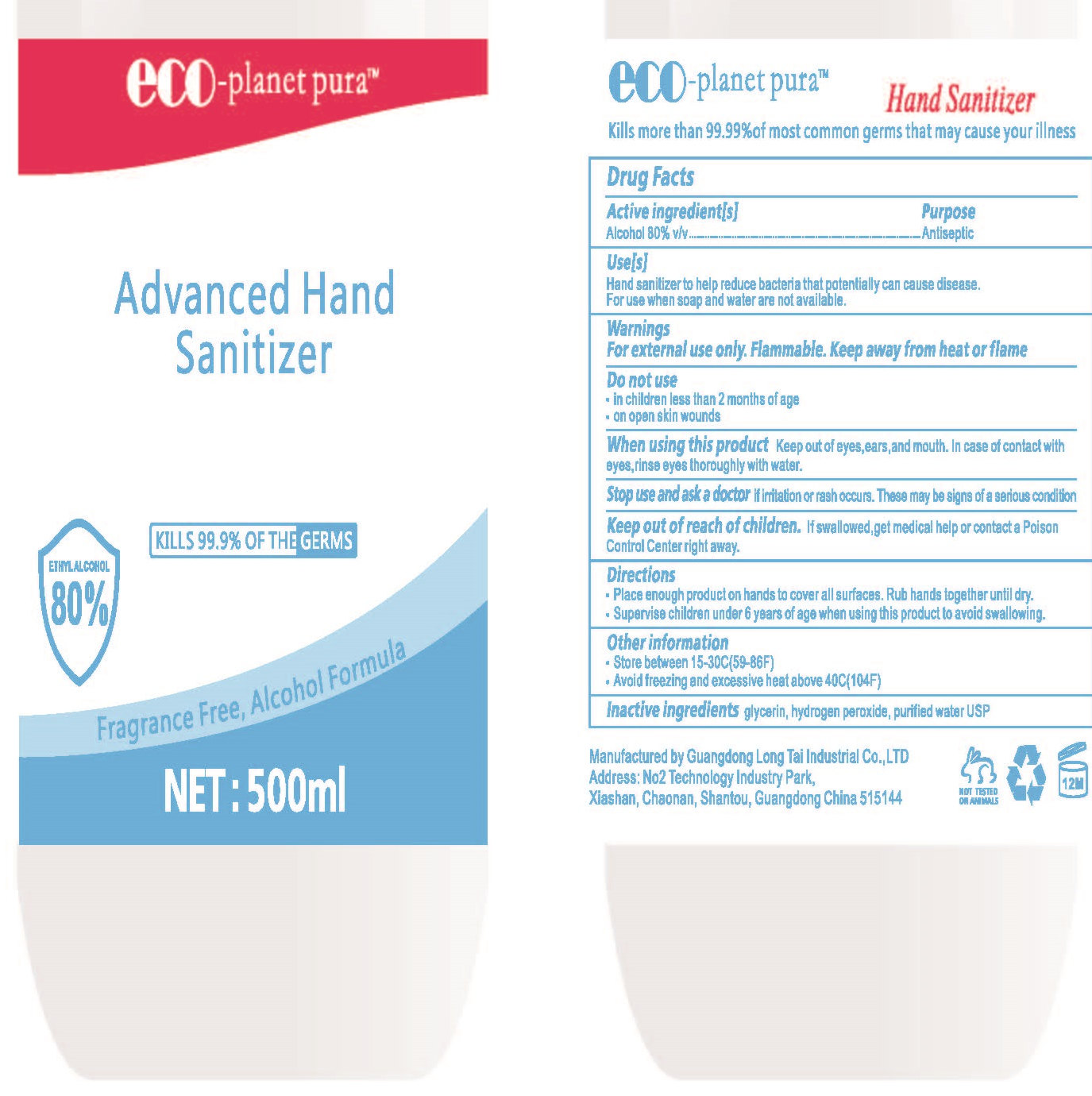 DRUG LABEL: hand Sanitizer
NDC: 52807-001 | Form: LIQUID
Manufacturer: Guangdong Longtai Industry Co.,Ltd.
Category: otc | Type: HUMAN OTC DRUG LABEL
Date: 20200415

ACTIVE INGREDIENTS: ALCOHOL 375 mL/500 mL
INACTIVE INGREDIENTS: WATER; GLYCERIN; HYDROGEN PEROXIDE

DOSAGE AND ADMINISTRATION

1.Store behween 15-30C(59-86F).
2.Avoidreezing and excessive heat above 40C(104F).

INACTIVE INGREDIENT

Glycerin,

hydrogen peroxide，

purified water

INDICATIONS AND USAGE

1.Place enoughproducton hands to cover alsurfaces. Rub hands toehuriliay,
2.Supervise children under 6 years of age when using this product to avoid swallowing.

ACTIVE INGREDIENT

Alcohol

keep out of children

PURPOSE

Disinfection
Sterilization

WARNINGS

For external use only. Flammable. Keep away from heat or flame.